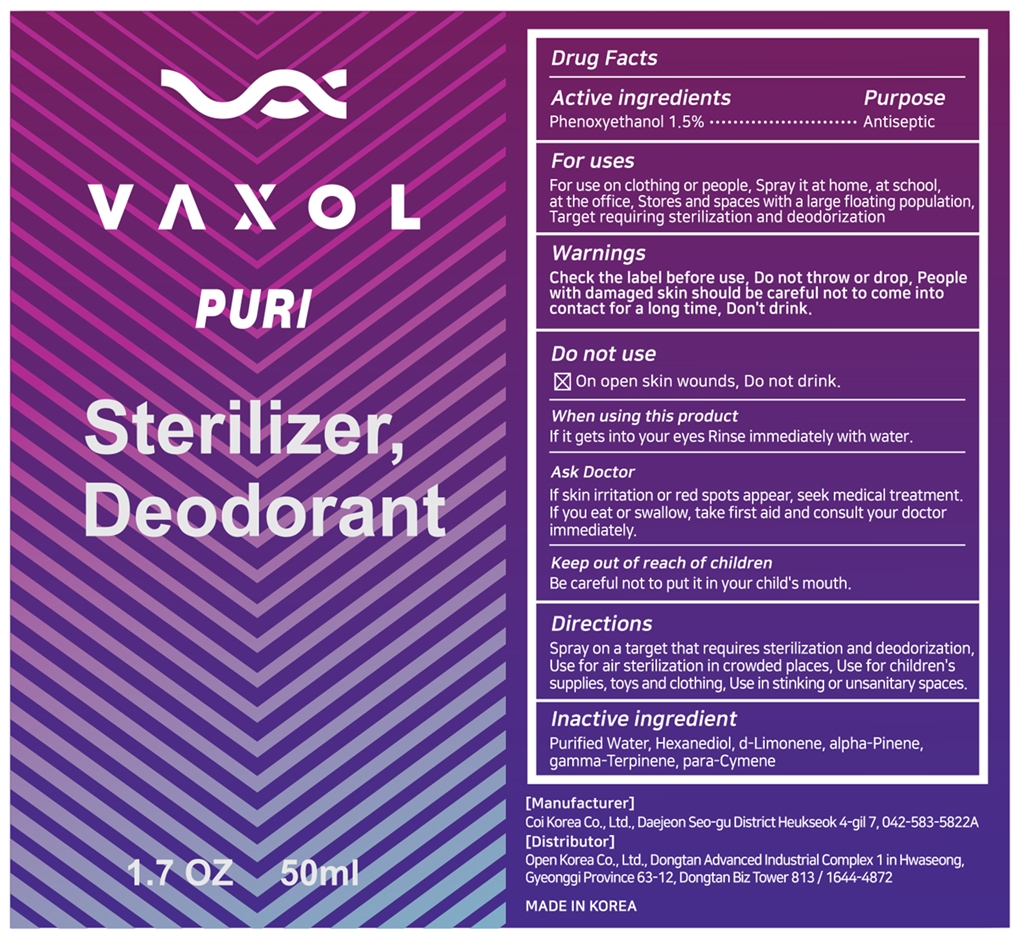 DRUG LABEL: VAXOL PURI
NDC: 81268-201 | Form: LIQUID
Manufacturer: OPENKOREA CO., Ltd
Category: otc | Type: HUMAN OTC DRUG LABEL
Date: 20211117

ACTIVE INGREDIENTS: PHENOXYETHANOL 1.5 mg/100 mL
INACTIVE INGREDIENTS: .GAMMA.-TERPINENE; WATER; P-CYMENE; HEXANEDIOL; .ALPHA.-PINENE; LIMONENE, (+)-

Active Ingredient

Phenoxyethanol 1.5%

Purpose

Antiseptic

Use

For use on clothing or people, Spray it at home, at school, at the office, Stores and spaces with a large floating population, Target requiring sterilization and deodorization.

Warnings

Check the label before use, Do not throw or drop, People with damaged skin should be careful not to come into contact for a long time, Don't drink.

Do not use

On open skin wounds, Do not drink.

When using this product

If it gets into your eyes Rinse immediately with water.

Ask Doctor

If skin irritation or red spots appear, seek medical treatment. If you eat or swallow, take first aid and consult your doctor immediately.

Keep out of reach of children

Be careful not to put it in your child's mouth.

Directions

Spray on a target that requires sterilization and deodorization, Use for air sterilization in crowded places, Use for children's supplies, toys and clothing, Use in stinking or unsanitary spaces.

Inactive ingredient

Purified Water, Hexanediol, d-Limonene, alpha-Pinene, gamma-Terpinene, para-Cymene